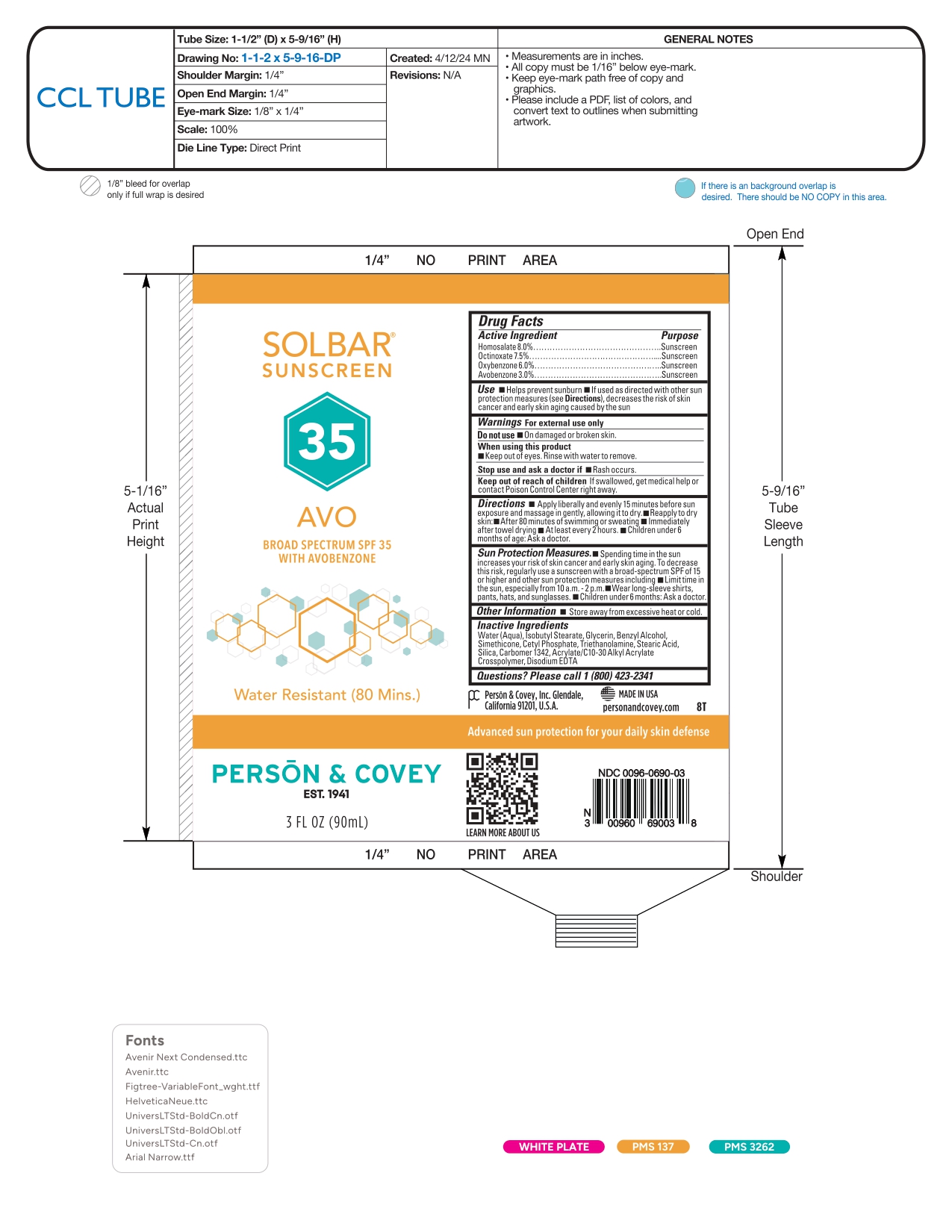 DRUG LABEL: SOLBAR SUNSCREEN 35 AVO
NDC: 0096-0690 | Form: CREAM
Manufacturer: Person and Covey
Category: otc | Type: HUMAN OTC DRUG LABEL
Date: 20260122

ACTIVE INGREDIENTS: HOMOSALATE 80 mg/1 g; OCTINOXATE 75 mg/1 g; AVOBENZONE 30 mg/1 g; OXYBENZONE 60 mg/1 g
INACTIVE INGREDIENTS: CARBOMER 1342; BENZYL ALCOHOL; TROLAMINE; ISOBUTYL STEARATE; CETYL PHOSPHATE; WATER; CARBOMER INTERPOLYMER TYPE A (ALLYL SUCROSE CROSSLINKED); GLYCERIN; STEARIC ACID; DIMETHICONE; EDETATE DISODIUM; SILICON DIOXIDE

SOLBAR AVO - sunscreen cream

Active ingredient

Homosalate 8.0%

Octinoxate 7.5%

Oxybenzone 6.0%

Avobenzone 3.0%

Purpose

Sunscreen

Uses

- Helps prevent sunburn.
- If used as directed with other sun protection measures (see Directions), decreases the risk of skin cancer and early skin aging caused by the sun.

Warnings

For external use only

Do not use on damaged or broken skin.

When using this product keep out of eyes. Rinse with water to remove.

Stop use and ask a doctor if rash occurs.

Keep out of reach of children

If swallowed, get medical help or contact a Poison Control Center right away.

Directions

- Apply liberally and evenly 15 minutes before sun exposure and massage in gently, allowing it to dry.
- Reapply to dry skin:
- After 80 minutes of swimming or sweating
- Immediately after towel drying
- At least every 2 hours
- Children under 6 months of age: Ask a doctor.

Sun Protection Measures.

- Spending time in the sun increases your risk of skin cancer and early skin aging. To decrease this risk, regularly use a sunscreen with a Broad Spectrum SPF value of 15 or higher and other sun protection measures including:
- Limit time in the sun, especially from 10 a.m. – 2 p.m.
- Wear long-sleeved shirts, pants, hats, and sunglasses.
- Children under 6 months of age: Ask a doctor.

Other Information

Store away from excessive heat or cold.

Inactive Ingredients

Water (Aqua), Isobutyl Stearate, Glycerin, Benzyl Alcohol, Simethicone, Cetyl Phosphate, Triethanolamine, Stearic Acid, Silica, Carbomer 1342, Acrylate/C10-30 Alkyl Acrylate Crosspolymer, Disodium EDTA

Questions?

Please call 1 (800) 423-2341

Company Information

Person & Covey, Inc. Glendale, California 91201, U.S.A. MADE IN USA personandcovey.com